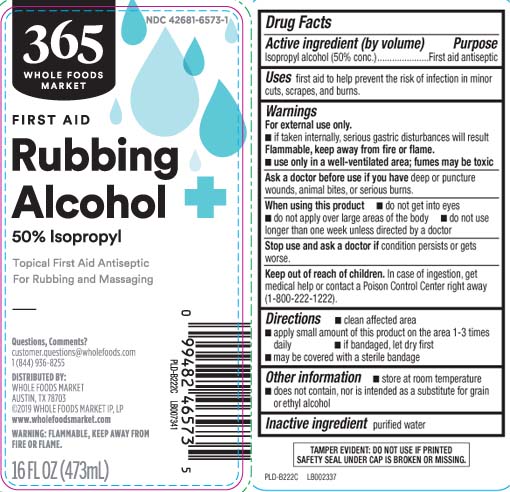 DRUG LABEL: 50 percent Isopropyl alcohol
NDC: 42681-6573 | Form: LIQUID
Manufacturer: Whole Foods Market
Category: otc | Type: HUMAN OTC DRUG LABEL
Date: 20250214

ACTIVE INGREDIENTS: ISOPROPYL ALCOHOL 50 mL/100 mL
INACTIVE INGREDIENTS: WATER

Drug Facts

Active ingredient (by volume)

Isopropyl alcohol (50% conc)

Purpose

first aid antiseptic

Uses

- first aid to help prevent the risk of infection in minor cuts, scrapes and burns

Warnings

For external use only.

- If taken internally, serious gastic disturbances will result

Flammable, keep away from fire or flame.

- use only in a well-ventilated area; fumes may be toxic

Ask a doctor before use if you have

- deep or puncture wounds, animal bites or serious burns

When using this product

- do not get into eyes
- do not apply over large areas of the body
- do not use longer than one week unless directed by a doctor

Stop use and ask a doctor if

- condition persists or gets worse

Keep out of reach of children.

In case of ingestion, get medical help or contact a Poison Control Center right away (1-800-222-1222).

Directions

- clean affected area
- apply small amount of this product on the area 1-3 times daily
- if bandaged, let dry first
- may be covered with a sterile bandage

Other information

- store at room temperature
- does not contain, nor is intended as a substitute for grain or ethyl alcohol

Inactive ingredients

purified water

Principal Display Panel

Rubbing Alcohol

50 % ISOPROPYL

+ FIRST AID +

- TOPICAL FIRST AID ANTISEPTIC
- FOR RUBBING & MASSAGING

WARNING: FLAMMABLE, KEEP AWAY FROM FIRE OR FLAME.

FL OZ (mL)

Questions, Comments?

customer,questions@wholefoods.com (512) 542-0878

DISTRIBUTED BY:

WHOLE FOODS MARKET

550 BOWIE STREET, AUSTIN, TX 78703

©2017 WHOLE FOODS MARKET IP, LP

www.wholefoodsmarket.com

TAMPER EVIDENT: DO NOT USE IF PRINTED SAFETY SEAL UNDER THE CAP IS BROKEN OR MISSING.

Package Label

WHOLE FOODS MARKET Rubbing Alcohol